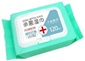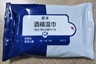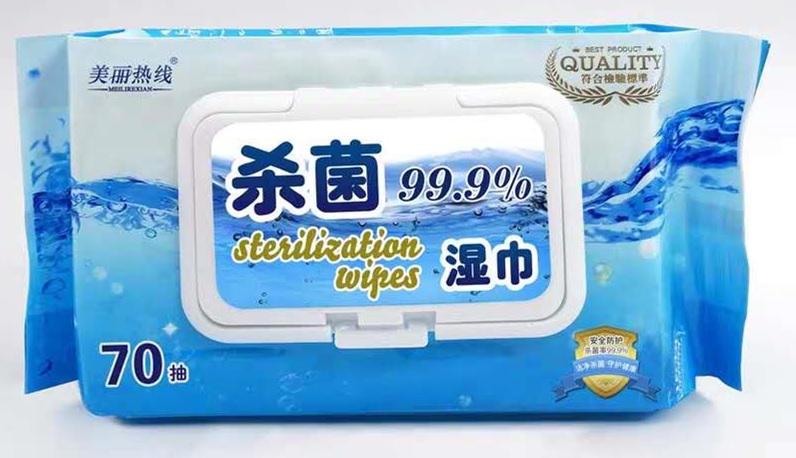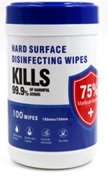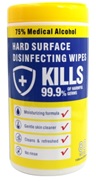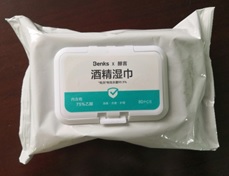 DRUG LABEL: Alcohol wet wipe
NDC: 75111-201 | Form: LIQUID
Manufacturer: Enping Jiaxin Daily Necessities Co., Ltd.
Category: otc | Type: HUMAN OTC DRUG LABEL
Date: 20200410

ACTIVE INGREDIENTS: ALCOHOL 0.75 mL/1 mL
INACTIVE INGREDIENTS: WATER

Alcohol wet wipe(75111-201)

Alcohol prep pad

Active Ingredient(s)

Alcohol 75% v/v. Purpose: Antiseptic

Purpose

Antiseptic

Use

Wipe the surface of the object to sterilize and disinfect

Warnings

For external use only. Flammable. Keep away from heat or flame

Do not use

- in children less than 2 months of age
- on open skin wounds

When using this product keep out of eyes, ears, and mouth. In case of contact with eyes, rinse eyes thoroughly with water.
Stop use and ask a doctor if irritation or rash occurs. These may be signs of a serious condition.
Keep out of reach of children. If swallowed, get medical help or contact a Poison Control Center right away.

Stop use and ask a doctor if irritation or rash occurs. These may be signs of a serious condition.

Keep out of reach of children. If swallowed, get medical help or contact a Poison Control Center right away.

Directions

- Wipe the surface of the object
- Supervise children under 6 years of age when using this product to avoid swallowing.

Other information

- Store between 15-30C (59-86F)
- Avoid freezing and excessive heat above 40C (104F)

Inactive ingredients

purified water USP

Package Label - Principal Display Panel

10 PCS/bag NDC: 75111-201-01

50 PCS/bag NDC: 75111-201-02

70 PCS/bag NDC: 75111-201-03

80 PCS/bag NDC: 75111-201-04

80 PCS/box NDC: 75111-201-05

100 PCS/box NDC: 75111-201-06

120 PCS/bag NDC: 75111-201-07